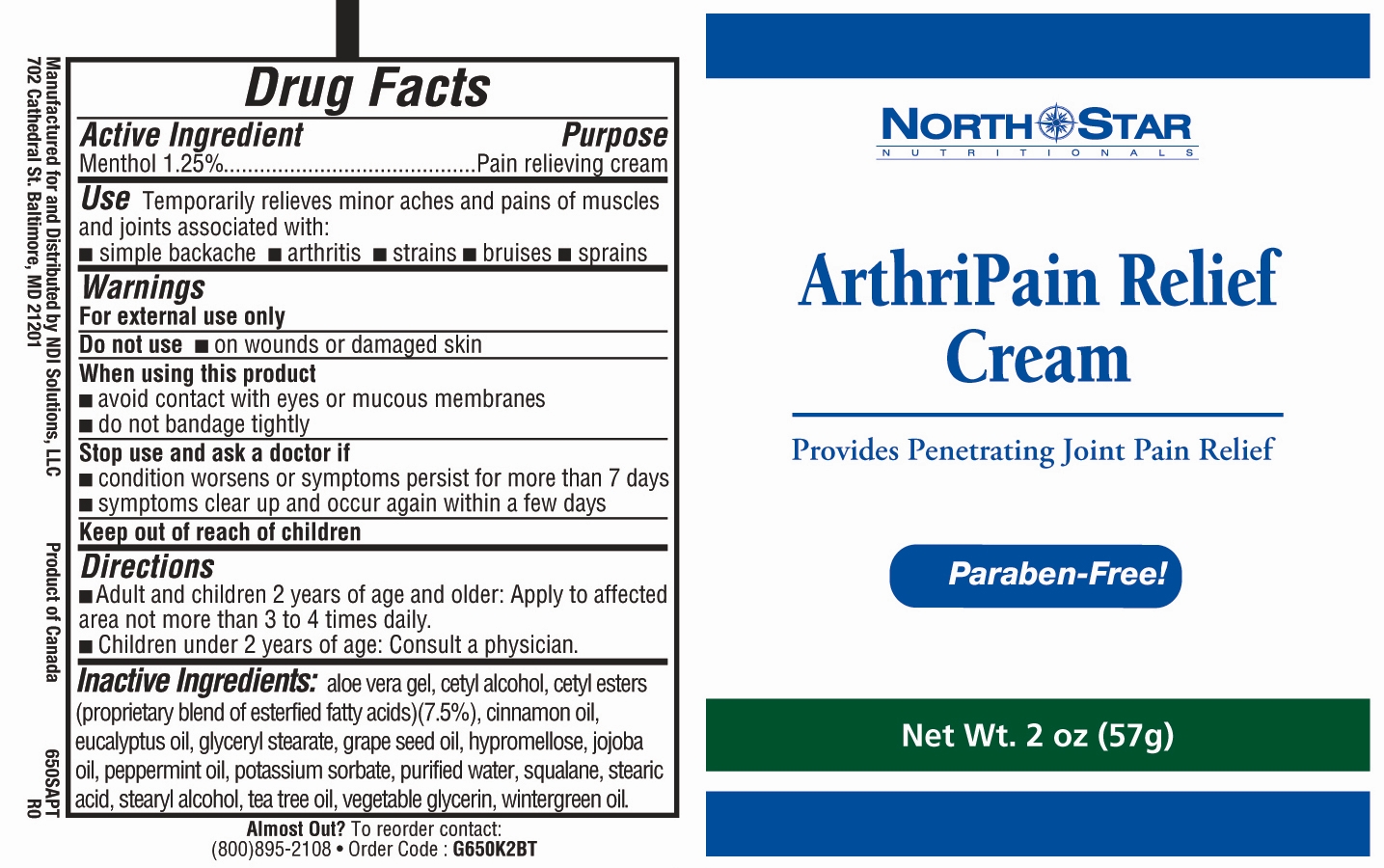 DRUG LABEL: ArthriPain Relief
NDC: 50972-278 | Form: CREAM
Manufacturer: NDI Solutions LLC
Category: otc | Type: HUMAN OTC DRUG LABEL
Date: 20100413

ACTIVE INGREDIENTS: Menthol 12.5 mg/1 g
INACTIVE INGREDIENTS: Aloe Vera Leaf; Cetyl Alcohol; Cetyl Esters Wax; Cinnamon Oil; EUCALYPTUS OIL; GLYCERYL MONOSTEARATE; GRAPE SEED OIL; HYPROMELLOSE; JOJOBA OIL; PEPPERMINT OIL; POTASSIUM SORBATE; WATER; SQUALANE; STEARIC ACID; STEARYL ALCOHOL; TEA TREE OIL; GLYCERIN; METHYL SALICYLATE

Drug Facts

Active Ingredient Purpose

Menthol 1.25%.................................................................Pain relieving cream

PURPOSE

Use Temporarily relieves minor aches and pains of muscles and joints associated with:

- simple backache
- arthritis
- strains
- bruises
- sprains

Warnings

For external use only

Do not use

- on wounds or damaged skin

When using this product

- avoid contact with eyes or mucous membranes
- do not bandage tightly

Stop use and ask a doctor if

- condition worsens or symptoms persist for more than 7 days
- symptoms clear up and occur again within a few days

Keep out of reach of children

Directions

- Adult and children 2 years of age and older: Apply to affected area not more than 3 to 4 times daily.
- Children under 2 years of age: Consult a physician.

INACTIVE INGREDIENT

Inactive Ingredients: aloe vera gel, cetyl alcohol, cetyl esters
(proprietary blend of esterfied fatty acids)(7.5%), cinnamon oil,
eucalyptus oil, glyceryl stearate, grape seed oil, hypromellose, jojoba
oil, peppermint oil, potassium sorbate, purified water, squalane, stearic
acid, stearyl alcohol, tea tree oil, vegetable glycerin, wintergreen oil.

PACKAGE LABEL

ArthriPain packaging